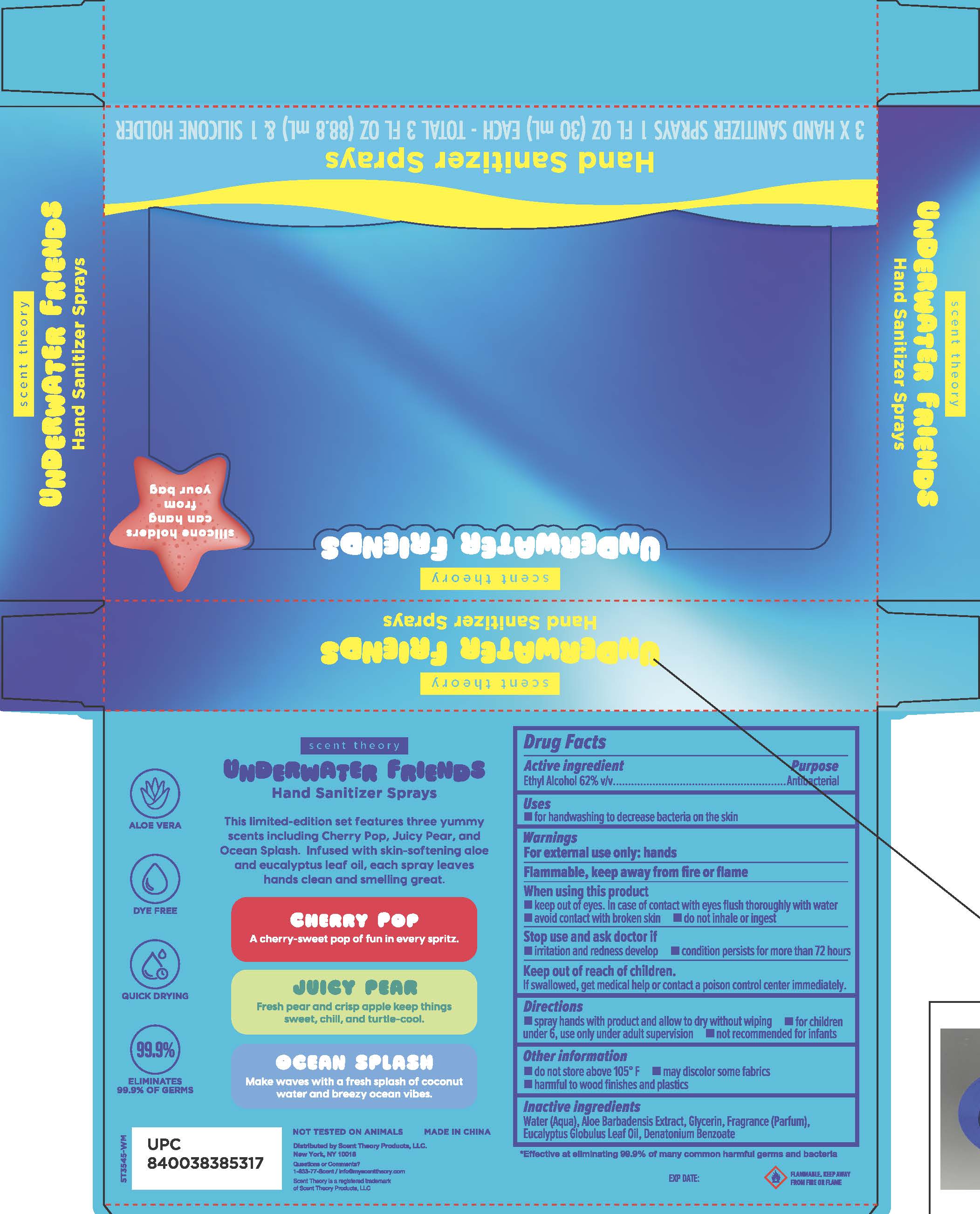 DRUG LABEL: Scent Theory Hand Sanitizers
NDC: 76891-168 | Form: SPRAY
Manufacturer: Scent Theory Products LLC
Category: otc | Type: HUMAN OTC DRUG LABEL
Date: 20260223

ACTIVE INGREDIENTS: ALCOHOL 62 mL/100 mL
INACTIVE INGREDIENTS: EUCALYPTUS GLOBULUS LEAF; GLYCERIN; WATER; ALOE VERA LEAF; DENATONIUM BENZOATE

Scent Theory Hand Sanitizer Sprays (Cherry Pop, Ocean Splash, Juicy Pear) 76891-168-03

Drug Facts

Active ingredients

Ethyl Alcohol 62% V/V

Purpose

Antibacterial

Uses

For handwashing to decrease bacteria on the skin.

Warnings

For external use only: hands
Flammable, keep away from fire or flame.

When using this product
- keep out of eyes. In case of contact with eyes, flush thoroughly with water.
- avoid contact with broken skin.
- do not inhale or ingest.

Stop use and ask a doctor if
- irritation and redness develop
- condition persists for more than 72 hours

keep out of reach of children.
If swallowed, get medical help or contact a poison control center right away.

Directions

Spray hands with product and allow to dry without wiping
For children under 6, use only under adult supervision
Not recommended for infants

Other information

Do not store above 105°F
may discolor some fabrics
harmful to wood finishes and plastics

Inactive ingredients

Water (Aqua), Aloe Barbadensis Extract, Glycerin, Fragrance (Parfum), Eucalyptus Globulus Leaf Oil, Denatonium Benzoate